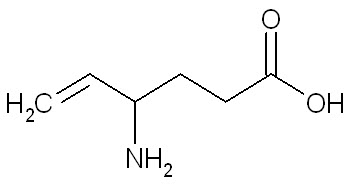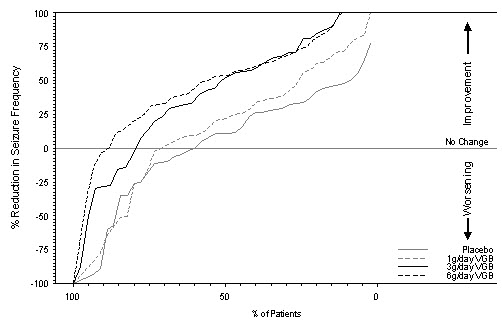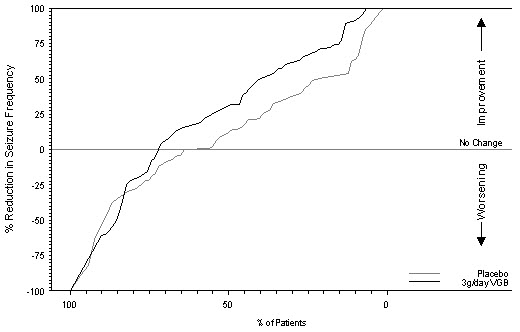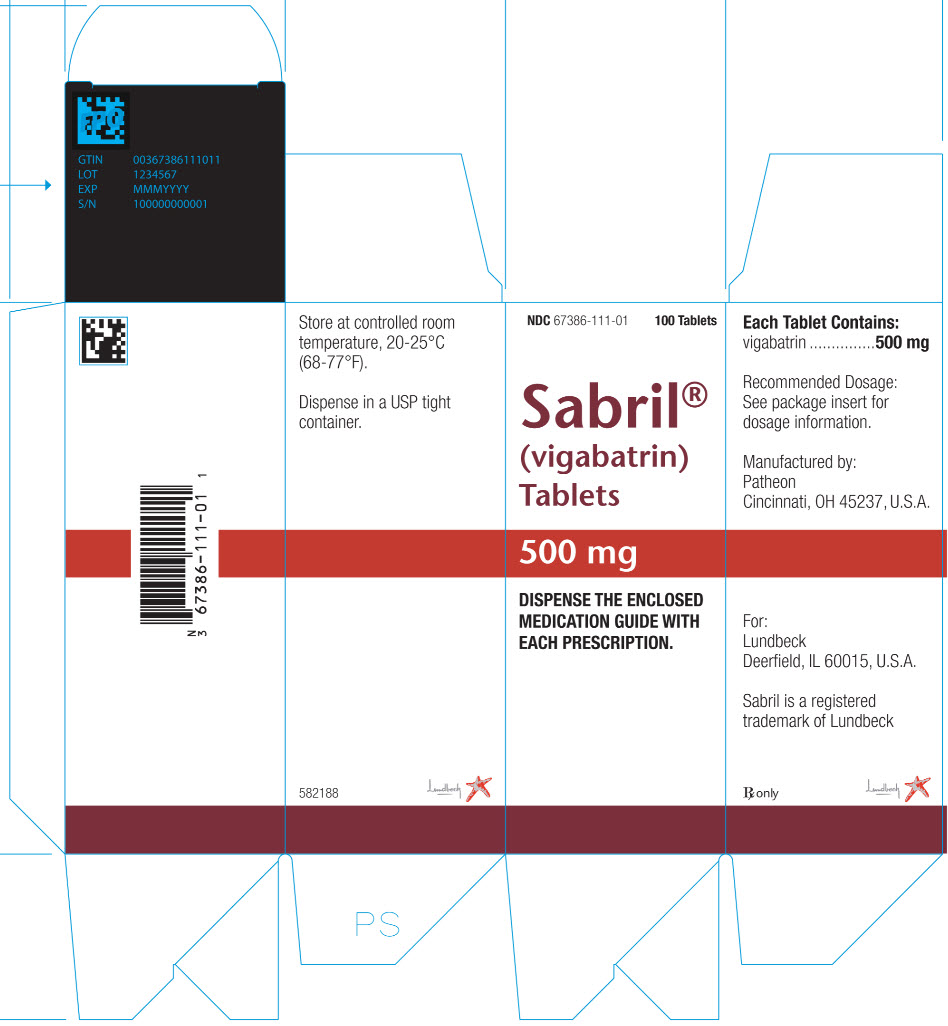 DRUG LABEL: SABRIL
NDC: 67386-111 | Form: TABLET, FILM COATED
Manufacturer: Lundbeck Pharmaceuticals LLC
Category: prescription | Type: HUMAN PRESCRIPTION DRUG LABEL
Date: 20211020

ACTIVE INGREDIENTS: VIGABATRIN 500 mg/1 1
INACTIVE INGREDIENTS: HYPROMELLOSES; MAGNESIUM STEARATE; CELLULOSE, MICROCRYSTALLINE; POLYETHYLENE GLYCOL, UNSPECIFIED; POVIDONE; TITANIUM DIOXIDE; SODIUM STARCH GLYCOLATE TYPE A POTATO

HIGHLIGHTS OF PRESCRIBING INFORMATION

These highlights do not include all the information needed to use SABRIL safely and effectively. See full prescribing information for SABRIL.
SABRIL® (vigabatrin) tablets, for oral use
SABRIL® (vigabatrin) for oral solution
Initial U.S. Approval: 2009

WARNING: PERMANENT VISION LOSS

See full prescribing information for complete boxed warning.

- SABRIL can cause permanent bilateral concentric visual field constriction, including tunnel vision that can result in disability. In some cases, SABRIL may also decrease visual acuity (5.1).
- Risk increases with increasing dose and cumulative exposure, but there is no dose or exposure to SABRIL known to be free of risk of vision loss (5.1).
- Risk of new and worsening vision loss continues as long as SABRIL is used, and possibly after discontinuing SABRIL (5.1).
- Baseline and periodic vision assessment is recommended for patients on SABRIL. However, this assessment cannot always prevent vision damage (5.1).
- SABRIL is available only through a restricted program called the Vigabatrin REMS Program (5.2).

1 INDICATIONS AND USAGE

SABRIL is indicated for the treatment of:

- Refractory Complex Partial Seizures as adjunctive therapy in patients 2 years of age and older who have responded inadequately to several alternative treatments; SABRIL is not indicated as a first line agent (1.1)
- Infantile Spasms - monotherapy in infants 1 month to 2 years of age for whom the potential benefits outweigh the potential risk of vision loss (1.2)

2 DOSAGE AND ADMINISTRATION

Refractory Complex Partial Seizures

- Adults (17 years of age and older): Initiate at 1000 mg/day (500 mg twice daily); increase total daily dose weekly in 500 mg/day increments, to the recommended dose of 3000 mg/day (1500 mg twice daily) (2.2)
- Pediatric (2 to 16 years of age): The recommended dosage is based on body weight and administered as two divided doses (2.2)
- The dosage may be increased in weekly intervals, depending on response (2.2)
- Dose patients weighing more than 60 kg according to adult recommendations (2.2)

Infantile Spasms

- Initiate at a daily dose of 50 mg/kg (25 mg/kg twice daily); increase total daily dose every 3 days, in increments of 25 mg/kg/day to 50 mg/kg/day, up to a maximum daily dose of 150 mg/kg (75 mg/kg twice daily) (2.3)

Renal Impairment: Dose adjustment recommended (2.4, 8.5, 8.6)

3 DOSAGE FORMS AND STRENGTHS

- Tablet: 500 mg (3)
- For oral solution: 500 mg per packet (3)

4 CONTRAINDICATIONS

None (4)

5 WARNINGS AND PRECAUTIONS

- Abnormal MRI signal changes and intramyelinic edema have been reported in some infants with Infantile Spasms receiving SABRIL (5.3, 5.4)
- Suicidal behavior and ideation: Antiepileptic drugs, including SABRIL, increase the risk of suicidal thoughts and behavior (5.5)
- Withdrawal of AEDs: Taper dose to avoid withdrawal seizures (5.6)
- Anemia: Monitor for symptoms of anemia (5.7)
- Somnolence and fatigue: Advise patients not to drive or operate machinery until they have gained sufficient experience on SABRIL (5.8)

6 ADVERSE REACTIONS

Refractory Complex Partial Seizures

Most common adverse reactions in controlled studies include (incidence ≥5% over placebo):

- Adults: blurred vision, somnolence, dizziness, abnormal coordination, tremor, and fatigue (6.1)
- Pediatric patients (3 to 16 years of age): weight gain (6.1)

Infantile Spasms (incidence >5% and greater than on placebo)

- Somnolence, bronchitis, ear infection, and acute otitis media (6.1)

To report SUSPECTED ADVERSE REACTIONS, contact Lundbeck at 1-800-455-1141 or FDA at 1-800-FDA-1088 or www.fda.gov/medwatch.

7 DRUG INTERACTIONS

Decreased phenytoin plasma levels: dosage adjustment may be needed (7.1)

8 USE IN SPECIFIC POPULATIONS

- Pregnancy: Based on animal data, may cause fetal harm. (8.1)
- Lactation: SABRIL is excreted in human milk (8.2)

FULL PRESCRIBING INFORMATION

WARNING: PERMANENT VISION LOSS

- SABRIL can cause permanent bilateral concentric visual field constriction including tunnel vision that can result in disability. In some cases, SABRIL also can damage the central retina and may decrease visual acuity [see Warnings and Precautions (5.1)].
- The onset of vision loss from SABRIL is unpredictable, and can occur within weeks of starting treatment or sooner, or at any time after starting treatment, even after months or years.
- Symptoms of vision loss from SABRIL are unlikely to be recognized by patients or caregivers before vision loss is severe. Vision loss of milder severity, while often unrecognized by the patient or caregiver, can still adversely affect function.
- The risk of vision loss increases with increasing dose and cumulative exposure, but there is no dose or exposure known to be free of risk of vision loss.
- Vision assessment is recommended at baseline (no later than 4 weeks after starting SABRIL), at least every 3 months during therapy, and about 3 to 6 months after the discontinuation of therapy.
- Once detected, vision loss due to SABRIL is not reversible. It is expected that, even with frequent monitoring, some patients will develop severe vision loss.
- Consider drug discontinuation, balancing benefit and risk, if visual loss is documented.
- Risk of new or worsening vision loss continues as long as SABRIL is used. It is possible that vision loss can worsen despite discontinuation of SABRIL.
- Because of the risk of visual loss, SABRIL should be withdrawn from patients with refractory complex partial seizures who fail to show substantial clinical benefit within 3 months of initiation and within 2-4 weeks of initiation for patients with infantile spasms, or sooner if treatment failure becomes obvious. Patient response to and continued need for SABRIL should be periodically reassessed.
- SABRIL should not be used in patients with, or at high risk of, other types of irreversible vision loss unless the benefits of treatment clearly outweigh the risks.
- SABRIL should not be used with other drugs associated with serious adverse ophthalmic effects such as retinopathy or glaucoma unless the benefits clearly outweigh the risks.
- Use the lowest dosage and shortest exposure to SABRIL consistent with clinical objectives [see Dosage and Administration (2.1)].

Because of the risk of permanent vision loss, SABRIL is available only through a restricted program under a Risk Evaluation and Mitigation Strategy (REMS) called the Vigabatrin REMS Program [see Warnings and Precautions (5.2)]. Further information is available at www.vigabatrinREMS.com or 1-866-244-8175.

1 INDICATIONS AND USAGE

1.1 Refractory Complex Partial Seizures (CPS)

SABRIL is indicated as adjunctive therapy for adults and pediatric patients 2 years of age and older with refractory complex partial seizures who have inadequately responded to several alternative treatments and for whom the potential benefits outweigh the risk of vision loss [see Warnings and Precautions (5.1)]. SABRIL is not indicated as a first line agent for complex partial seizures.

1.2 Infantile Spasms (IS)

SABRIL is indicated as monotherapy for pediatric patients with infantile spasms 1 month to 2 years of age for whom the potential benefits outweigh the potential risk of vision loss [see Warnings and Precautions (5.1)].

2 DOSAGE AND ADMINISTRATION

2.1 Important Dosing and Administration Instructions

Dosing

Use the lowest dosage and shortest exposure to SABRIL consistent with clinical objectives [see Warnings and Precautions (5.1)].

The SABRIL dosing regimen depends on the indication, age group, weight, and dosage form (tablets or for oral solution) [see Dosage and Administration (2.2, 2.3)]. Patients with impaired renal function require dose adjustment [see Dosage and Administration (2.4)].

Monitoring of SABRIL plasma concentrations to optimize therapy is not helpful.

Administration

SABRIL is given orally with or without food.

SABRIL for oral solution should be mixed with water prior to administration [see Dosage and Administration (2.5)]. A calibrated measuring device is recommended to measure and deliver the prescribed dose accurately. A household teaspoon or tablespoon is not an adequate measuring device.

If a decision is made to discontinue SABRIL, the dose should be gradually reduced [see Dosage and Administration (2.2, 2.3) and Warnings and Precautions (5.6)].

2.2 Refractory Complex Partial Seizures

Adults (Patients 17 Years of Age and Older)
Treatment should be initiated at 1000 mg/day (500 mg twice daily). Total daily dose may be increased in 500 mg increments at weekly intervals depending on response. The recommended dose of SABRIL in adults is 3000 mg/day (1500 mg twice daily). A 6000 mg/day dose has not been shown to confer additional benefit compared to the 3000 mg/day dose and is associated with an increased incidence of adverse events.

In controlled clinical studies in adults with complex partial seizures, SABRIL was tapered by decreasing the daily dose 1000 mg/day on a weekly basis until discontinued [see Warnings and Precautions (5.6)].

Pediatric (Patients 2 to 16 Years of Age)

The recommended dosage is based on body weight and administered as two divided doses, as shown in Table 1. The dosage may be increased in weekly intervals to the total daily maintenance dosage, depending on response.

Pediatric patients weighing more than 60 kg should be dosed according to adult recommendations.

Table 1. CPS Dosing Recommendations for Pediatric Patients Weighing 10 kg up to 60 kg††
Body Weight; [kg] | Total Daily*; Starting Dose; [mg/day] | Total Daily*; Maintenance Dose†; [mg/day]
10 kg to 15 kg | 350 mg | 1050 mg
Greater than 15 kg to 20 kg | 450 mg | 1300 mg
Greater than 20 kg to 25 kg | 500 mg | 1500 mg
Greater than 25 kg to 60 kg | 500 mg | 2000 mg
* Administered in two divided doses; † Maintenance dose is based on 3000 mg/day adult-equivalent dose; †† Patients weighing more than 60 kg should be dosed according to adult recommendations

In patients with refractory complex partial seizures, SABRIL should be withdrawn if a substantial clinical benefit is not observed within 3 months of initiating treatment. If, in the clinical judgment of the prescriber, evidence of treatment failure becomes obvious earlier than 3 months, treatment should be discontinued at that time [see Warnings and Precautions (5.1)].

In a controlled study in pediatric patients with complex partial seizures, SABRIL was tapered by decreasing the daily dose by one third every week for three weeks [see Warnings and Precautions (5.6)].

2.3 Infantile Spasms

The initial daily dosing is 50 mg/kg/day given in two divided doses (25 mg/kg twice daily); subsequent dosing can be titrated by 25 mg/kg/day to 50 mg/kg/day increments every 3 days, up to a maximum of 150 mg/kg/day given in 2 divided doses (75 mg/kg twice daily) [see Use in Specific Populations (8.4)].

Table 2 provides the volume of the 50 mg/mL dosing solution that should be administered as individual doses in infants of various weights.

Table 2. Infant Dosing Table
Weight [kg] | Starting Dose 50 mg/kg/day |  | Maximum Dose 150 mg/kg/day
3 | 1.5 mL twice daily |  | 4.5 mL twice daily
4 | 2 mL twice daily |  | 6 mL twice daily
5 | 2.5 mL twice daily |  | 7.5 mL twice daily
6 | 3 mL twice daily |  | 9 mL twice daily
7 | 3.5 mL twice daily |  | 10.5 mL twice daily
8 | 4 mL twice daily |  | 12 mL twice daily
9 | 4.5 mL twice daily |  | 13.5 mL twice daily
10 | 5 mL twice daily |  | 15 mL twice daily
11 | 5.5 mL twice daily |  | 16.5 mL twice daily
12 | 6 mL twice daily |  | 18 mL twice daily
13 | 6.5 mL twice daily |  | 19.5 mL twice daily
14 | 7 mL twice daily |  | 21 mL twice daily
15 | 7.5 mL twice daily |  | 22.5 mL twice daily
16 | 8 mL twice daily |  | 24 mL twice daily

In patients with infantile spasms, SABRIL should be withdrawn if a substantial clinical benefit is not observed within 2 to 4 weeks. If, in the clinical judgment of the prescriber, evidence of treatment failure becomes obvious earlier than 2 to 4 weeks, treatment should be discontinued at that time [see Warnings and Precautions (5.1)].

In a controlled clinical study in patients with infantile spasms, SABRIL was tapered by decreasing the daily dose at a rate of 25 mg/kg to 50 mg/kg every 3 to 4 days [see Warnings and Precautions (5.6)].

2.4 Patients with Renal Impairment

SABRIL is primarily eliminated through the kidney.

Infants
Information about how to adjust the dose in infants with renal impairment is unavailable.

Adult and pediatric patients 2 years and older

- Mild renal impairment (CLcr >50 to 80 mL/min): dose should be decreased by 25%
- Moderate renal impairment (CLcr >30 to 50 mL/min): dose should be decreased by 50%
- Severe renal impairment (CLcr >10 to 30 mL/min): dose should be decreased by 75%

CLcr in mL/min may be estimated from serum creatinine (mg/dL) using the following formulas:

- Patients 2 to <12 years old: CLcr (mL/min/1.73 m^2) = (K × Ht) / Scr

height (Ht) in cm; serum creatinine (Scr) in mg/dL
K (proportionality constant): Female Child (<12 years): K=0.55;
Male Child (<12 years): K=0.70

- Adult and pediatric patients 12 years or older: CLcr (mL/min) = [140-age (years)] × weight (kg) / [72 × serum creatinine (mg/dL)] (× 0.85 for female patients)

The effect of dialysis on SABRIL clearance has not been adequately studied [see Clinical Pharmacology (12.3) and Use in Specific Populations (8.6)].

2.5 Preparation and Administration Instructions for SABRIL for oral solution

If using SABRIL for oral solution, physicians should review and discuss the Medication Guide and instructions for mixing and giving SABRIL with the patient or caregiver(s). Physicians should confirm that patients or caregiver(s) understand how to mix SABRIL powder with water and administer the correct daily dose.

Empty the entire contents of each 500 mg packet into a clean cup, and dissolve in 10 mL of cold or room temperature water per packet. Administer the resulting solution using the 3 mL or 10 mL oral syringe provided by the pharmacy [see How Supplied/Storage and Handling (16.1)]. The concentration of the final solution is 50 mg/mL.

Table 3 below describes how many packets and how many milliliters (mL) of water will be needed to prepare each individual dose. The concentration after reconstitution is 50 mg/mL.

Table 3. Number of SABRIL Packets and mL of Water Needed for Each Individual Dose
Individual Dose [mg]; [Given Twice Daily] | Total Number of; SABRIL Packets | Total mL of Water; Required for Dissolving
0 to 500 | 1 Packet | 10 mL
501 to 1000 | 2 Packets | 20 mL
1001 to 1500 | 3 Packets | 30 mL

Discard the resulting solution if it is not clear (or free of particles) and colorless. Each individual dose should be prepared and used immediately. Discard any unused portion of the solution after administering the correct dose.

3 DOSAGE FORMS AND STRENGTHS

Tablet: 500 mg: white, oval, film-coated, biconvex, scored on one side, and debossed with OV 111 on the other.

For oral solution: 500 mg packet containing a white to off-white granular powder.

4 CONTRAINDICATIONS

None.

5 WARNINGS AND PRECAUTIONS

5.1 Permanent Vision Loss

SABRIL can cause permanent vision loss. Because of this risk and because, when it is effective, SABRIL provides an observable symptomatic benefit; patient response and continued need for treatment should be periodically assessed.

Based upon adult studies, 30 percent or more of patients can be affected with bilateral concentric visual field constriction ranging in severity from mild to severe. Severe cases may be characterized by tunnel vision to within 10 degrees of visual fixation, which can result in disability. In some cases, SABRIL also can damage the central retina and may decrease visual acuity. Symptoms of vision loss from SABRIL are unlikely to be recognized by patients or caregivers before vision loss is severe. Vision loss of milder severity, while often unrecognized by the patient or caregiver, can still adversely affect function.

Because assessing vision may be difficult in infants and children, the frequency and extent of vision loss is poorly characterized in these patients. For this reason, the understanding of the risk is primarily based on the adult experience. The possibility that vision loss from SABRIL may be more common, more severe, or have more severe functional consequences in infants and children than in adults cannot be excluded.

The onset of vision loss from SABRIL is unpredictable and can occur within weeks of starting treatment or sooner, or at any time after starting treatment, even after months or years.

The risk of vision loss increases with increasing dose and cumulative exposure, but there is no dose or exposure known to be free of risk of vision loss.

In patients with refractory complex partial seizures, SABRIL should be withdrawn if a substantial clinical benefit is not observed within 3 months of initiating treatment. If, in the clinical judgment of the prescriber, evidence of treatment failure becomes obvious earlier than 3 months, treatment should be discontinued at that time [see Dosage and Administration (2.2) and Warnings and Precautions (5.6)].

In patients with infantile spasms, SABRIL should be withdrawn if a substantial clinical benefit is not observed within 2 to 4 weeks. If, in the clinical judgment of the prescriber, evidence of treatment failure becomes obvious earlier than 2 to 4 weeks, treatment should be discontinued at that time [see Dosage and Administration (2.3) and Warnings and Precautions (5.6)].

SABRIL should not be used in patients with, or at high risk of, other types of irreversible vision loss unless the benefits of treatment clearly outweigh the risks. The interaction of other types of irreversible vision damage with vision damage from SABRIL has not been well-characterized, but is likely adverse.

SABRIL should not be used with other drugs associated with serious adverse ophthalmic effects such as retinopathy or glaucoma unless the benefits clearly outweigh the risks.

Monitoring of Vision

Monitoring of vision by an ophthalmic professional with expertise in visual field interpretation and the ability to perform dilated indirect ophthalmoscopy of the retina is recommended [see Warnings and Precautions (5.2)]. Because vision testing in infants is difficult, vision loss may not be detected until it is severe. For patients receiving SABRIL, vision assessment is recommended at baseline (no later than 4 weeks after starting SABRIL), at least every 3 months while on therapy, and about 3-6 months after the discontinuation of therapy. The diagnostic approach should be individualized for the patient and clinical situation.

In adults and cooperative pediatric patients, perimetry is recommended, preferably by automated threshold visual field testing. Additional testing may also include electrophysiology (e.g., electroretinography [ERG]), retinal imaging (e.g., optical coherence tomography [OCT]), and/or other methods appropriate for the patient. In patients who cannot be tested, treatment may continue according to clinical judgment, with appropriate patient counseling. Because of variability, results from ophthalmic monitoring must be interpreted with caution, and repeat assessment is recommended if results are abnormal or uninterpretable. Repeat assessment in the first few weeks of treatment is recommended to establish if, and to what degree, reproducible results can be obtained, and to guide selection of appropriate ongoing monitoring for the patient.

The onset and progression of vision loss from SABRIL is unpredictable, and it may occur or worsen precipitously between assessments. Once detected, vision loss due to SABRIL is not reversible. It is expected that even with frequent monitoring, some SABRIL patients will develop severe vision loss. Consider drug discontinuation, balancing benefit and risk, if vision loss is documented. It is possible that vision loss can worsen despite discontinuation of SABRIL.

5.2 Vigabatrin REMS Program

SABRIL is available only through a restricted distribution program called the Vigabatrin REMS Program, because of the risk of permanent vision loss.

Notable requirements of the Vigabatrin REMS Program include the following:

- Prescribers must be certified by enrolling in the program, agreeing to counsel patients on the risk of vision loss and the need for periodic monitoring of vision, and reporting any event suggestive of vision loss to Lundbeck.
- Patients must enroll in the program.
- Pharmacies must be certified and must only dispense to patients authorized to receive SABRIL.

Further information is available at www.vigabatrinREMS.com, or call 1-866-244-8175.

5.3 Magnetic Resonance Imaging (MRI) Abnormalities in Infants

Abnormal MRI signal changes characterized by increased T2 signal and restricted diffusion in a symmetric pattern involving the thalamus, basal ganglia, brain stem, and cerebellum have been observed in some infants treated with vigabatrin.

In a retrospective epidemiologic study in infants with infantile spasms (N=205), the prevalence of MRI changes was 22% in vigabatrin-treated patients versus 4% in patients treated with other therapies. In this study, in post marketing experience, and in published literature reports, these changes generally resolved with discontinuation of treatment. In a few patients, the lesion resolved despite continued use. It has been reported that some infants exhibited coincident motor abnormalities, but no causal relationship has been established and the potential for long-term clinical sequelae has not been adequately studied.

Neurotoxicity (brain histopathology and neurobehavioral abnormalities) was observed in rats exposed to vigabatrin during late gestation and the neonatal and juvenile periods of development, and brain histopathological changes were observed in dogs exposed to vigabatrin during the juvenile period of development. The relationship between these findings and the abnormal MRI findings in infants treated with vigabatrin for infantile spasms is unknown [see Warnings and Precautions (5.4) and Use in Specific Populations (8.1)].

The specific pattern of signal changes observed in patients 6 years and younger was not observed in older pediatric and adult patients treated with vigabatrin. In a blinded review of MRI images obtained in prospective clinical trials in patients with refractory complex partial seizures (CPS) 3 years and older (N=656), no difference was observed in anatomic distribution or prevalence of MRI signal changes between vigabatrin treated and placebo treated patients. In the postmarketing setting, MRI changes have also been reported in patients 6 years of age and younger being treated for refractory CPS.

For adults treated with SABRIL, routine MRI surveillance is unnecessary as there is no evidence that vigabatrin causes MRI changes in this population.

5.4 Neurotoxicity

Intramyelinic Edema (IME) has been reported in postmortem examination of infants being treated for infantile spasms with vigabatrin.

Abnormal MRI signal changes characterized by increased T2 signal and restricted diffusion in a symmetric pattern involving the thalamus, basal ganglia, brain stem, and cerebellum have also been observed in some infants treated for IS with vigabatrin. Studies of the effects of vigabatrin on MRI and evoked potentials (EP) in adult epilepsy patients have demonstrated no clear-cut abnormalities [see Warnings and Precautions (5.3)].

Vacuolation, characterized by fluid accumulation and separation of the outer layers of myelin, has been observed in brain white matter tracts in adult and juvenile rats and adult mice, dogs, and possibly monkeys following administration of vigabatrin. This lesion, referred to as intramyelinic edema (IME), was seen in animals at doses within the human therapeutic range. A no-effect dose was not established in rodents or dogs. In the rat and dog, vacuolation was reversible following discontinuation of vigabatrin treatment, but, in the rat, pathologic changes consisting of swollen or degenerating axons, mineralization, and gliosis were seen in brain areas in which vacuolation had been previously observed. Vacuolation in adult animals was correlated with alterations in MRI and changes in visual and somatosensory EP.

Administration of vigabatrin to rats during the neonatal and juvenile periods of development produced vacuolar changes in the brain gray matter (including the thalamus, midbrain, deep cerebellar nuclei, substantia nigra, hippocampus, and forebrain) which are considered distinct from the IME observed in vigabatrin treated adult animals. Decreased myelination and evidence of oligodendrocyte injury were additional findings in the brains of vigabatrin-treated rats. An increase in apoptosis was seen in some brain regions following vigabatrin exposure during the early postnatal period. Long-term neurobehavioral abnormalities (convulsions, neuromotor impairment, learning deficits) were also observed following vigabatrin treatment of young rats. Administration of vigabatrin to juvenile dogs produced vacuolar changes in the brain gray matter (including the septal nuclei, hippocampus, hypothalamus, thalamus, cerebellum, and globus pallidus). Neurobehavioral effects of vigabatrin were not assessed in the juvenile dog. These effects in young animals occurred at doses lower than those producing neurotoxicity in adult animals and were associated with plasma vigabatrin levels substantially lower than those achieved clinically in infants and children [see Use in Specific Populations (8.1, 8.4)].

In a published study, vigabatrin (200, 400 mg/kg/day) induced apoptotic neurodegeneration in the brain of young rats when administered by intraperitoneal injection on postnatal days 5-7.

Administration of vigabatrin to female rats during pregnancy and lactation at doses below those used clinically resulted in hippocampal vacuolation and convulsions in the mature offspring.

5.5 Suicidal Behavior and Ideation

Antiepileptic drugs (AEDs), including SABRIL, increase the risk of suicidal thoughts or behavior in patients taking these drugs for any indication. Patients treated with any AED for any indication should be monitored for the emergence or worsening of depression, suicidal thoughts or behavior, and/or any unusual changes in mood or behavior.

Pooled analyses of 199 placebo-controlled clinical trials (mono- and adjunctive therapy) of 11 different AEDs showed that patients randomized to one of the AEDs had approximately twice the risk (adjusted Relative Risk 1.8, 95% CI: 1.2, 2.7) of suicidal thinking or behavior compared to patients randomized to placebo. In these trials, which had a median treatment duration of 12 weeks, the estimated incidence rate of suicidal behavior or ideation among 27,863 AED treated patients was 0.43%, compared to 0.24% among 16,029 placebo-treated patients, representing an increase of approximately one case of suicidal thinking or behavior for every 530 patients treated. There were four suicides in drug treated patients in the trials and none in placebo treated patients, but the number is too small to allow any conclusion about drug effect on suicide.

The increased risk of suicidal thoughts or behavior with AEDs was observed as early as one week after starting drug treatment with AEDs and persisted for the duration of treatment assessed. Because most trials included in the analysis did not extend beyond 24 weeks, the risk of suicidal thoughts or behavior beyond 24 weeks could not be assessed.

The risk of suicidal thoughts or behavior was generally consistent among drugs in the data analyzed. The finding of increased risk with AEDs of varying mechanisms of action and across a range of indications suggests that the risk applies to all AEDs used for any indication. The risk did not vary substantially by age (5-100 years) in the clinical trials analyzed. Table 4 shows absolute and relative risk by indication for all evaluated AEDs.

Table 4. Risk by Indication for Antiepileptic Drugs in the Pooled Analysis
Indication | Placebo Patients with Events per 1000 Patients | Drug Patients with Events per 1000 Patients | Relative Risk: Incidence of Drug Events in Drug Patients/Incidence in Placebo Patients | Risk Difference: Additional Drug Patients with Events per 1000 Patients
Epilepsy | 1.0 | 3.4 | 3.5 | 2.4
Psychiatric | 5.7 | 8.5 | 1.5 | 2.9
Other | 1.0 | 1.8 | 1.9 | 0.9
Total | 2.4 | 4.3 | 1.8 | 1.9

The relative risk for suicidal thoughts or behavior was higher in clinical trials for epilepsy than in clinical trials for psychiatric or other conditions, but the absolute risk differences were similar for the epilepsy and psychiatric indications.

Anyone considering prescribing SABRIL or any other AED must balance the risk of suicidal thoughts or behavior with the risk of untreated illness. Epilepsy and many other illnesses for which AEDs are prescribed are themselves associated with morbidity and mortality and an increased risk of suicidal thoughts and behavior. Should suicidal thoughts and behavior emerge during treatment, the prescriber needs to consider whether the emergence of these symptoms in any given patient may be related to the illness being treated.

Patients, their caregivers, and families should be informed that AEDs increase the risk of suicidal thoughts and behavior and should be advised of the need to be alert for the emergence or worsening of the signs and symptoms of depression, any unusual changes in mood or behavior, or the emergence of suicidal thoughts, behavior, or thoughts about self-harm. Behaviors of concern should be reported immediately to healthcare providers.

5.6 Withdrawal of Antiepileptic Drugs (AEDs)

As with all AEDs, SABRIL should be withdrawn gradually. However, if withdrawal is needed because of a serious adverse event, rapid discontinuation can be considered. Patients and caregivers should be told not to suddenly discontinue SABRIL therapy.

In controlled clinical studies in adults with complex partial seizures, SABRIL was tapered by decreasing the daily dose 1000 mg/day on a weekly basis until discontinued.

In a controlled study in pediatric patients with complex partial seizures, SABRIL was tapered by decreasing the daily dose by one third every week for three weeks.

In a controlled clinical study in patients with infantile spasms, SABRIL was tapered by decreasing the daily dose at a rate of 25-50 mg/kg every 3-4 days.

5.7 Anemia

In North American controlled trials in adults, 6% of patients (16/280) receiving SABRIL and 2% of patients (3/188) receiving placebo had adverse events of anemia and/or met criteria for potentially clinically important hematology changes involving hemoglobin, hematocrit, and/or RBC indices. Across U.S. controlled trials, there were mean decreases in hemoglobin of about 3% and 0% in SABRIL and placebo-treated patients, respectively, and a mean decrease in hematocrit of about 1% in SABRIL-treated patients compared to a mean gain of about 1% in patients treated with placebo.

In controlled and open-label epilepsy trials in adults and pediatric patients, 3 SABRIL patients (0.06%, 3/4855) discontinued for anemia and 2 SABRIL patients experienced unexplained declines in hemoglobin to below 8 g/dL and/or hematocrit below 24%.

5.8 Somnolence and Fatigue

SABRIL causes somnolence and fatigue. Patients should be advised not to drive a car or operate other complex machinery until they are familiar with the effects of SABRIL on their ability to perform such activities.

Pooled data from two SABRIL controlled trials in adults demonstrated that 24% (54/222) of SABRIL patients experienced somnolence compared to 10% (14/135) of placebo patients. In those same studies, 28% of SABRIL patients experienced fatigue compared to 15% (20/135) of placebo patients. Almost 1% of SABRIL patients discontinued from clinical trials for somnolence and almost 1% discontinued for fatigue.

Pooled data from three SABRIL controlled trials in pediatric patients demonstrated that 6% (10/165) of SABRIL patients experienced somnolence compared to 5% (5/104) of placebo patients. In those same studies, 10% (17/165) of SABRIL patients experienced fatigue compared to 7% (7/104) of placebo patients. No SABRIL patients discontinued from clinical trials due to somnolence or fatigue.

5.9 Peripheral Neuropathy

SABRIL causes symptoms of peripheral neuropathy in adults. Pediatric clinical trials were not designed to assess symptoms of peripheral neuropathy, but observed incidence of symptoms based on pooled data from controlled pediatric studies appeared similar for pediatric patients on vigabatrin and placebo. In a pool of North American controlled and uncontrolled epilepsy studies, 4.2% (19/457) of SABRIL patients developed signs and/or symptoms of peripheral neuropathy. In the subset of North American placebo-controlled epilepsy trials, 1.4% (4/280) of SABRIL treated patients and no (0/188) placebo patients developed signs and/or symptoms of peripheral neuropathy. Initial manifestations of peripheral neuropathy in these trials included, in some combination, symptoms of numbness or tingling in the toes or feet, signs of reduced distal lower limb vibration or position sensation, or progressive loss of reflexes, starting at the ankles. Clinical studies in the development program were not designed to investigate peripheral neuropathy systematically and did not include nerve conduction studies, quantitative sensory testing, or skin or nerve biopsy. There is insufficient evidence to determine if development of these signs and symptoms was related to duration of SABRIL treatment, cumulative dose, or if the findings of peripheral neuropathy were completely reversible upon discontinuation of SABRIL.

5.10 Weight Gain

SABRIL causes weight gain in adult and pediatric patients.

Data pooled from randomized controlled trials in adults found that 17% (77/443) of SABRIL patients versus 8% (22/275) of placebo patients gained ≥7% of baseline body weight. In these same trials, the mean weight change among SABRIL patients was 3.5 kg compared to 1.6 kg for placebo patients.

Data pooled from randomized controlled trials in pediatric patients with refractory complex partial seizures found that 47% (77/163) of SABRIL patients versus 19% (19/102) of placebo patients gained ≥7% of baseline body weight.

In all epilepsy trials, 0.6% (31/4855) of SABRIL patients discontinued for weight gain. The long term effects of SABRIL related weight gain are not known. Weight gain was not related to the occurrence of edema.

5.11 Edema

SABRIL causes edema in adults. Pediatric clinical trials were not designed to assess edema, but observed incidence of edema-based pooled data from controlled pediatric studies appeared similar for pediatric patients on vigabatrin and placebo.

Pooled data from controlled trials demonstrated increased risk among SABRIL patients compared to placebo patients for peripheral edema (SABRIL 2%, placebo 1%), and edema (SABRIL 1%, placebo 0%). In these studies, one SABRIL and no placebo patients discontinued for an edema related AE. In adults, there was no apparent association between edema and cardiovascular adverse events such as hypertension or congestive heart failure. Edema was not associated with laboratory changes suggestive of deterioration in renal or hepatic function.

6 ADVERSE REACTIONS

The following serious and otherwise important adverse reactions are described elsewhere in labeling:

- Permanent Vision Loss [see BOXED WARNING and Warnings and Precautions (5.1)]
- Magnetic Resonance Imaging (MRI) Abnormalities in Infants [see Warnings and Precautions (5.3)]
- Neurotoxicity [see Warnings and Precautions (5.4)]
- Suicidal Behavior and Ideation [see Warnings and Precautions (5.5)]
- Withdrawal of Antiepileptic Drugs (AEDs) [see Warnings and Precautions (5.6)]
- Anemia [see Warnings and Precautions (5.7)]
- Somnolence and Fatigue [see Warnings and Precautions (5.8)]
- Peripheral Neuropathy [see Warnings and Precautions (5.9)]
- Weight Gain [see Warnings and Precautions (5.10)]
- Edema [see Warnings and Precautions (5.11)]

6.1 Clinical Trial Experience

Because clinical trials are conducted under widely varying conditions, adverse reaction rates observed in the clinical trials of a drug cannot be directly compared to rates in the clinical trials of another drug and may not reflect the rates observed in practice.

In U.S. and primary non-U.S. clinical studies of 4,079 SABRIL-treated patients, the most common (≥5%) adverse reactions associated with the use of SABRIL in combination with other AEDs were headache, somnolence, fatigue, dizziness, convulsion, nasopharyngitis, weight gain, upper respiratory tract infection, visual field defect, depression, tremor, nystagmus, nausea, diarrhea, memory impairment, insomnia, irritability, abnormal coordination, blurred vision, diplopia, vomiting, influenza, pyrexia, and rash.

The adverse reactions most commonly associated with SABRIL treatment discontinuation in ≥1% of patients were convulsion and depression.

In patients with infantile spasms, the adverse reactions most commonly associated with SABRIL treatment discontinuation in ≥1% of patients were infections, status epilepticus, developmental coordination disorder, dystonia, hypotonia, hypertonia, weight gain, and insomnia.

Refractory Complex Partial Seizures
Adults
Table 5 lists the adverse reactions that occurred in ≥2% and more than one patient per SABRIL-treated group and that occurred more frequently than in placebo patients from 2 U.S. adjunctive clinical studies of refractory CPS in adults.

Table 5. Adverse Reactions in Pooled, Adjunctive Trials in Adults with Refractory Complex Partial Seizures
 | SABRIL dosage (mg/day)
Body System Adverse Reaction | 3000 [N=134] % | 6000 [N=43] % | Placebo [N=135] %
Ear Disorders
Tinnitus | 2 | 0 | 1
Vertigo | 2 | 5 | 1
Eye Disorders
Blurred vision | 13 | 16 | 5
Diplopia | 7 | 16 | 3
Asthenopia | 2 | 2 | 0
Eye pain | 0 | 5 | 0
Gastrointestinal Disorders
Diarrhea | 10 | 16 | 7
Nausea | 10 | 2 | 8
Vomiting | 7 | 9 | 6
Constipation | 8 | 5 | 3
Upper abdominal pain | 5 | 5 | 1
Dyspepsia | 4 | 5 | 3
Stomach discomfort | 4 | 2 | 1
Abdominal pain | 3 | 2 | 1
Toothache | 2 | 5 | 2
Abdominal distension | 2 | 0 | 1
General Disorders
Fatigue | 23 | 40 | 16
Gait disturbance | 6 | 12 | 7
Asthenia | 5 | 7 | 1
Edema peripheral | 5 | 7 | 1
Fever | 4 | 7 | 3
Chest pain | 1 | 5 | 1
Thirst | 2 | 0 | 0
Malaise | 0 | 5 | 0
Infections
Nasopharyngitis | 14 | 9 | 10
Upper respiratory tract infection | 7 | 9 | 6
Influenza | 5 | 7 | 4
Urinary tract infection | 4 | 5 | 0
Bronchitis | 0 | 5 | 1
Injury
Contusion | 3 | 5 | 2
Joint sprain | 1 | 2 | 1
Muscle strain | 1 | 2 | 1
Wound secretion | 0 | 2 | 0
Metabolism and Nutrition Disorders
Increased appetite | 1 | 5 | 1
Weight gain | 6 | 14 | 3
Musculoskeletal Disorders
Arthralgia | 10 | 5 | 3
Back pain | 4 | 7 | 2
Pain in extremity | 6 | 2 | 4
Myalgia | 3 | 5 | 1
Muscle twitching | 1 | 9 | 1
Muscle spasms | 3 | 0 | 1
Nervous System Disorders
Headache | 33 | 26 | 31
Somnolence | 22 | 26 | 13
Dizziness | 24 | 26 | 17
Nystagmus | 13 | 19 | 9
Tremor | 15 | 16 | 8
Memory impairment | 7 | 16 | 3
Abnormal coordination | 7 | 16 | 2
Disturbance in attention | 9 | 0 | 1
Sensory disturbance | 4 | 7 | 2
Hyporeflexia | 4 | 5 | 1
Paraesthesia | 7 | 2 | 1
Lethargy | 4 | 7 | 2
Hyperreflexia | 4 | 2 | 3
Hypoaesthesia | 4 | 5 | 1
Sedation | 4 | 0 | 0
Status epilepticus | 2 | 5 | 0
Dysarthria | 2 | 2 | 1
Postictal state | 2 | 0 | 1
Sensory loss | 0 | 5 | 0
Psychiatric Disorders
Irritability | 7 | 23 | 7
Depression | 6 | 14 | 3
Confusional state | 4 | 14 | 1
Anxiety | 4 | 0 | 3
Depressed mood | 5 | 0 | 1
Abnormal thinking | 3 | 7 | 0
Abnormal behavior | 3 | 5 | 1
Expressive language disorder | 1 | 7 | 1
Nervousness | 2 | 5 | 2
Abnormal dreams | 1 | 5 | 1
Reproductive System
Dysmenorrhea | 9 | 5 | 3
Erectile dysfunction | 0 | 5 | 0
Respiratory and Thoracic Disorders
Pharyngolaryngeal pain | 7 | 14 | 5
Cough | 2 | 14 | 7
Pulmonary congestion | 0 | 5 | 1
Sinus headache | 6 | 2 | 1
Skin and Subcutaneous Tissue Disorders
Rash | 4 | 5 | 4

Pediatrics 2 to 16 years of age
Table 6 lists adverse reactions from controlled clinical studies of pediatric patients receiving SABRIL or placebo as adjunctive therapy for refractory complex partial seizures. Adverse reactions that are listed occurred in at least 2% of SABRIL-treated patients and more frequently than placebo. The median SABRIL dose was 49.4 mg/kg (range of 8.0 – 105.9 mg/kg).

Table 6. Adverse Reactions in Pooled, Adjunctive Trials in Pediatric Patients 3 to 16 Years of Age with Refractory Complex Partial Seizures
Body System; Adverse Reaction | All SABRIL [N=165] % | Placebo [N=104] %
Eye Disorders
Diplopia | 3 | 2
Blurred vision | 2 | 0
Gastrointestinal Disorders
Upper abdominal pain | 4 | 3
Constipation | 2 | 1
General Disorders
Fatigue | 10 | 7
Infections and Infestations
Upper respiratory tract infection | 15 | 11
Influenza | 7 | 3
Otitis media | 6 | 4
Streptococcal pharyngitis | 4 | 3
Viral gastroenteritis | 2 | 0
Investigations
Weight gain | 15 | 2
Nervous System Disorders
Somnolence | 6 | 5
Nystagmus | 4 | 3
Tremor | 4 | 2
Status epilepticus | 2 | 1
Psychiatric Disorders
Abnormal behavior | 7 | 6
Aggression | 6 | 2
Disorientation | 3 | 0

Safety of SABRIL for the treatment of refractory CPS in patients 2 years of age is expected to be similar to pediatric patients 3 to 16 years of age.

Infantile Spasms
In a randomized, placebo-controlled IS study with a 5 day double-blind treatment phase (n=40), the adverse reactions that occurred in >5% of patients receiving SABRIL and that occurred more frequently than in placebo patients were somnolence (SABRIL 45%, placebo 30%), bronchitis (SABRIL 30%, placebo 15%), ear infection (SABRIL 10%, placebo 5%), and acute otitis media (SABRIL 10%, placebo 0%).

In a dose response study of low-dose (18-36 mg/kg/day) versus high-dose (100-148 mg/kg/day) SABRIL, no clear correlation between dose and incidence of adverse reactions was observed. The adverse reactions (≥5% in either dose group) are summarized in Table 7.

Table 7. Adverse Reactions in a Placebo-Controlled Trial in Patients with Infantile Spasms
 | SABRIL Low Dose | SABRIL High Dose
Body System Adverse Reaction | [N=114] % | [N=108] %
Eye Disorders (other than field or acuity changes)
Strabismus | 5 | 5
Conjunctivitis | 5 | 2
Gastrointestinal Disorders
Vomiting | 14 | 20
Constipation | 14 | 12
Diarrhea | 13 | 12
General Disorders
Fever | 29 | 19
Infections
Upper respiratory tract infection | 51 | 46
Otitis media | 44 | 30
Viral infection | 20 | 19
Pneumonia | 13 | 11
Candidiasis | 8 | 3
Ear infection | 7 | 14
Gastroenteritis viral | 6 | 5
Sinusitis | 5 | 9
Urinary tract infection | 5 | 6
Influenza | 5 | 3
Croup infectious | 5 | 1
Metabolism & Nutrition Disorders
Decreased appetite | 9 | 7
Nervous System Disorders
Sedation | 19 | 17
Somnolence | 17 | 19
Status epilepticus | 6 | 4
Lethargy | 5 | 7
Convulsion | 4 | 7
Hypotonia | 4 | 6
Psychiatric Disorders
Irritability | 16 | 23
Insomnia | 10 | 12
Respiratory Disorders
Nasal congestion | 13 | 4
Cough | 3 | 8
Skin and Subcutaneous Tissue Disorders
Rash | 8 | 11

6.2 Postmarketing Experience

The following adverse reactions have been identified during postapproval use of SABRIL. Because these reactions are reported voluntarily from a population of uncertain size, it is not always possible to reliably estimate their frequency or establish a causal relationship to drug exposure. Adverse reactions are categorized by system organ class.

Birth Defects: Congenital cardiac defects, congenital external ear anomaly, congenital hemangioma, congenital hydronephrosis, congenital male genital malformation, congenital oral malformation, congenital vesicoureteric reflux, dentofacial anomaly, dysmorphism, fetal anticonvulsant syndrome, hamartomas, hip dysplasia, limb malformation, limb reduction defect, low set ears, renal aplasia, retinitis pigmentosa, supernumerary nipple, talipes

Ear Disorders: Deafness

Endocrine Disorders: Delayed puberty

Gastrointestinal Disorders: Gastrointestinal hemorrhage, esophagitis

General Disorders: Developmental delay, facial edema, malignant hyperthermia, multi-organ failure

Hepatobiliary Disorders: Cholestasis

Nervous System Disorders: Dystonia, encephalopathy, hypertonia, hypotonia, muscle spasticity, myoclonus, optic neuritis, dyskinesia

Psychiatric Disorders: Acute psychosis, apathy, delirium, hypomania, neonatal agitation, psychotic disorder

Respiratory Disorders: Laryngeal edema, pulmonary embolism, respiratory failure, stridor

Skin and Subcutaneous Tissue Disorders: Angioedema, maculo-papular rash, pruritus, Stevens-Johnson syndrome (SJS), toxic epidermal necrolysis (TEN), alopecia

7 DRUG INTERACTIONS

7.1 Antiepileptic Drugs

Phenytoin
Although phenytoin dose adjustments are not routinely required, dose adjustment of phenytoin should be considered if clinically indicated, since SABRIL may cause a moderate reduction in total phenytoin plasma levels [see Clinical Pharmacology (12.3)].

Clonazepam
SABRIL may moderately increase the Cmax of clonazepam resulting in an increase of clonazepam-associated adverse reactions [see Clinical Pharmacology (12.3)].

Other AEDs
There are no clinically significant pharmacokinetic interactions between SABRIL and either phenobarbital or sodium valproate. Based on population pharmacokinetics, carbamazepine, clorazepate, primidone, and sodium valproate appear to have no effect on plasma concentrations of vigabatrin [see Clinical Pharmacology (12.3)].

7.2 Oral Contraceptives

SABRIL is unlikely to affect the efficacy of steroid oral contraceptives [see Clinical Pharmacology (12.3)].

7.3 Drug-Laboratory Test Interactions

SABRIL decreases alanine transaminase (ALT) and aspartate transaminase (AST) plasma activity in up to 90% of patients. In some patients, these enzymes become undetectable. The suppression of ALT and AST activity by SABRIL may preclude the use of these markers, especially ALT, to detect early hepatic injury.

SABRIL may increase the amount of amino acids in the urine, possibly leading to a false positive test for certain rare genetic metabolic diseases (e.g., alpha aminoadipic aciduria).

8 USE IN SPECIFIC POPULATIONS

8.1 Pregnancy

Pregnancy Exposure Registry

There is a pregnancy exposure registry that monitors pregnancy outcomes in women exposed to AEDs, including SABRIL, during pregnancy. Encourage women who are taking SABRIL during pregnancy to enroll in the North American Antiepileptic Drug (NAAED) Pregnancy Registry. This can be done by calling the toll-free number 1-888-233-2334 or visiting the website, http://www.aedpregnancyregistry.org/. This must be done by the patient herself.

Risk Summary

There are no adequate data on the developmental risk associated with the use of SABRIL in pregnant women. Limited available data from case reports and cohort studies pertaining to SABRIL use in pregnant women have not established a drug-associated risk of major birth defects, miscarriage, or adverse maternal or fetal outcomes. However, based on animal data, SABRIL use in pregnant women may result in fetal harm.

When administered to pregnant animals, vigabatrin produced developmental toxicity, including an increase in fetal malformations and offspring neurobehavioral and neurohistopathological effects, at clinically relevant doses. In addition, developmental neurotoxicity was observed in rats treated with vigabatrin during a period of postnatal development corresponding to the third trimester of human pregnancy (see Data).

In the U.S. general population, the estimated background risk of major birth defects and miscarriage in clinically recognized pregnancies is 2-4% and 15-20%, respectively. The background risk of major birth defects and miscarriage for the indicated population is unknown.

Data

Animal Data

Administration of vigabatrin (oral doses of 50 to 200 mg/kg/day) to pregnant rabbits throughout the period of organogenesis was associated with an increased incidence of malformations (cleft palate) and embryofetal death; these findings were observed in two separate studies. The no-effect dose for adverse effects on embryofetal development in rabbits (100 mg/kg/day) is approximately 1/2 the maximum recommended human dose (MRHD) of 3 g/day on a body surface area (mg/m^2) basis. In rats, oral administration of vigabatrin (50, 100, or 150 mg/kg/day) throughout organogenesis resulted in decreased fetal body weights and increased incidences of fetal anatomic variations. The no-effect dose for adverse effects on embryo-fetal development in rats (50 mg/kg/day) is approximately 1/5 the MRHD on a mg/m^2 basis. Oral administration of vigabatrin (50, 100, 150 mg/kg/day) to rats from the latter part of pregnancy through weaning produced long-term neurohistopathological (hippocampal vacuolation) and neurobehavioral (convulsions) abnormalities in the offspring. A no-effect dose for developmental neurotoxicity in rats was not established; the low-effect dose (50 mg/kg/day) is approximately 1/5 the MRHD on a mg/m^2 basis.

In a published study, vigabatrin (300 or 450 mg/kg) was administered by intraperitoneal injection to a mutant mouse strain on a single day during organogenesis (day 7, 8, 9, 10, 11, or 12). An increase in fetal malformations (including cleft palate) was observed at both doses.

Oral administration of vigabatrin (5, 15, or 50 mg/kg/day) to young rats during the neonatal and juvenile periods of development (postnatal days 4-65) produced neurobehavioral (convulsions, neuromotor impairment, learning deficits) and neurohistopathological (brain vacuolation, decreased myelination, and retinal dysplasia) abnormalities in treated animals. The early postnatal period in rats is generally thought to correspond to late pregnancy in humans in terms of brain development. The no-effect dose for developmental neurotoxicity in juvenile rats (5 mg/kg/day) was associated with plasma vigabatrin exposures (AUC) less than 1/30 of those measured in pediatric patients receiving an oral dose of 50 mg/kg.

8.2 Lactation

Risk Summary

Vigabatrin is excreted in human milk. The effects of SABRIL on the breastfed infant and on milk production are unknown. Because of the potential for serious adverse reactions from vigabatrin in nursing infants, breastfeeding is not recommended. If exposing a breastfed infant to SABRIL, observe for any potential adverse effects [see Warnings and Precautions (5.1, 5.3, 5.4, 5.8)].

8.4 Pediatric Use

The safety and effectiveness of SABRIL as adjunctive treatment of refractory complex partial seizures in pediatric patients 2 to 16 years of age have been established and is supported by three double-blind, placebo-controlled studies in patients 3 to 16 years of age, adequate and well-controlled studies in adult patients, pharmacokinetic data from patients 2 years of age and older, and additional safety information in patients 2 years of age [see Clinical Pharmacology (12.3) and Clinical Studies (14.1)]. The dosing recommendation in this population varies according to age group and is weight-based [see Dosage and Administration (2.2)]. Adverse reactions in this pediatric population are similar to those observed in the adult population [see Adverse Reactions (6.1)]. The safety and effectiveness of SABRIL as monotherapy for pediatric patients with infantile spasms (1 month to 2 years of age) have been established [see Dosage and Administration (2.3) and Clinical Studies (14.2)].

Safety and effectiveness as adjunctive treatment of refractory complex partial seizures in pediatric patients below the age of 2 and as monotherapy for the treatment of infantile spasms in pediatric patients below the age of 1 month have not been established.

Duration of therapy for infantile spasms was evaluated in a post hoc analysis of a Canadian Pediatric Epilepsy Network (CPEN) study of developmental outcomes in infantile spasms patients. This analysis suggests that a total duration of 6 months of vigabatrin therapy is adequate for the treatment of infantile spasms. However, prescribers must use their clinical judgment as to the most appropriate duration of use [see Clinical Studies (14.2)].

Abnormal MRI signal changes and Intramyelinic Edema (IME) in infants and young children being treated with SABRIL have been observed [see Warnings and Precautions (5.3, 5.4)].

Juvenile Animal Toxicity Data

Oral administration of vigabatrin (5, 15, or 50 mg/kg/day) to young rats during the neonatal and juvenile periods of development (postnatal days 4-65) produced neurobehavioral (convulsions, neuromotor impairment, learning deficits) and neurohistopathological (brain gray matter vacuolation, decreased myelination, and retinal dysplasia) abnormalities. The no-effect dose for developmental neurotoxicity in juvenile rats (the lowest dose tested) was associated with plasma vigabatrin exposures (AUC) substantially less than those measured in pediatric patients at recommended doses. In dogs, oral administration of vigabatrin (30 or 100 mg/kg/day) during selected periods of juvenile development (postnatal days 22-112) produced neurohistopathological abnormalities (brain gray matter vacuolation). Neurobehavioral effects of vigabatrin were not assessed in the juvenile dog. A no-effect dose for neurohistopathology was not established in juvenile dogs; the lowest effect dose (30 mg/kg/day) was associated with plasma vigabatrin exposures lower than those measured in pediatric patients at recommended doses [see Warnings and Precautions (5.4)].

8.5 Geriatric Use

Clinical studies of vigabatrin did not include sufficient numbers of patients aged 65 and over to determine whether they responded differently from younger patients.

Vigabatrin is known to be substantially excreted by the kidney, and the risk of toxic reactions to this drug may be greater in patients with impaired renal function. Because elderly patients are more likely to have decreased renal function, care should be taken in dose selection, and it may be useful to monitor renal function.

Oral administration of a single dose of 1.5 g of vigabatrin to elderly (≥65 years) patients with reduced creatinine clearance (<50 mL/min) was associated with moderate to severe sedation and confusion in 4 of 5 patients, lasting up to 5 days. The renal clearance of vigabatrin was 36% lower in healthy elderly subjects (≥65 years) than in young healthy males. Adjustment of dose or frequency of administration should be considered. Such patients may respond to a lower maintenance dose [see Dosage and Administration (2.4) and Clinical Pharmacology (12.3)].

Other reported clinical experience has not identified differences in responses between the elderly and younger patients.

8.6 Renal Impairment

Dose adjustment, including initiating treatment with a lower dose, is necessary in pediatric patients 2 years of age and older and adults with mild (creatinine clearance >50 to 80 mL/min), moderate (creatinine clearance >30 to 50 mL/min) and severe (creatinine clearance >10 to 30 mL/min) renal impairment [see Dosage and Administration (2.4) and Clinical Pharmacology (12.3)].

9 DRUG ABUSE AND DEPENDENCE

9.1 Controlled Substance

Vigabatrin is not a controlled substance.

9.2 Abuse

Vigabatrin did not produce adverse events or overt behaviors associated with abuse when administered to humans or animals. It is not possible to predict the extent to which a CNS active drug will be misused, diverted, and/or abused once marketed. Consequently, physicians should carefully evaluate patients for history of drug abuse and follow such patients closely, observing them for signs of misuse or abuse of vigabatrin (e.g., incrementation of dose, drug-seeking behavior).

9.3 Dependence

Following chronic administration of vigabatrin to animals, there were no apparent withdrawal signs upon drug discontinuation. However, as with all AEDs, vigabatrin should be withdrawn gradually to minimize increased seizure frequency [see Warnings and Precautions (5.6)].

10 OVERDOSAGE

10.1 Signs, Symptoms, and Laboratory Findings of Overdosage

Confirmed and/or suspected vigabatrin overdoses have been reported during clinical trials and in post marketing surveillance. No vigabatrin overdoses resulted in death. When reported, the vigabatrin dose ingested ranged from 3 g to 90 g, but most were between 7.5 g and 30 g. Nearly half the cases involved multiple drug ingestions including carbamazepine, barbiturates, benzodiazepines, lamotrigine, valproic acid, acetaminophen, and/or chlorpheniramine.

Coma, unconsciousness, and/or drowsiness were described in the majority of cases of vigabatrin overdose. Other less commonly reported symptoms included vertigo, psychosis, apnea or respiratory depression, bradycardia, agitation, irritability, confusion, headache, hypotension, abnormal behavior, increased seizure activity, status epilepticus, and speech disorder. These symptoms resolved with supportive care.

10.2 Management of Overdosage

There is no specific antidote for SABRIL overdose. Standard measures to remove unabsorbed drug should be used, including elimination by emesis or gastric lavage. Supportive measures should be employed, including monitoring of vital signs and observation of the clinical status of the patient.

In an in vitro study, activated charcoal did not significantly adsorb vigabatrin.

The effectiveness of hemodialysis in the treatment of SABRIL overdose is unknown. In isolated case reports in renal failure patients receiving therapeutic doses of vigabatrin, hemodialysis reduced vigabatrin plasma concentrations by 40% to 60%.

11 DESCRIPTION

SABRIL (vigabatrin) is an oral antiepileptic drug and is available as white film-coated 500 mg tablets and as a white to off-white granular powder for oral solution in packets of 500 mg.

The chemical name of vigabatrin, a racemate consisting of two enantiomers, is (±) 4-amino-5-hexenoic acid. The molecular formula is C6H11NO2 and the molecular weight is 129.16. It has the following structural formula:

Vigabatrin is a white to off-white powder which is freely soluble in water, slightly soluble in methyl alcohol, very slightly soluble in ethyl alcohol and chloroform, and insoluble in toluene and hexane. The pH of a 1% aqueous solution is about 6.9. The n-octanol/water partition coefficient of vigabatrin is about 0.011 (log P=-1.96) at physiologic pH. Vigabatrin melts with decomposition in a 3-degree range within the temperature interval of 171ºC to 176ºC. The dissociation constants (pKa) of vigabatrin are 4 and 9.7 at room temperature (25ºC).

Each SABRIL tablet contains 500 mg of vigabatrin. The inactive ingredients are hydroxypropyl methylcellulose, magnesium stearate, microcrystalline cellulose, polyethylene glycols, povidone, sodium starch glycolate, and titanium dioxide.

SABRIL for oral solution is available as a white to off-white granular powder. Each packet contains 500 mg of vigabatrin. The inactive ingredient is povidone.

12 CLINICAL PHARMACOLOGY

12.1 Mechanism of Action

The precise mechanism of vigabatrin’s anti-seizure effect is unknown, but it is believed to be the result of its action as an irreversible inhibitor of γ-aminobutyric acid transaminase (GABA-T), the enzyme responsible for the metabolism of the inhibitory neurotransmitter GABA. This action results in increased levels of GABA in the central nervous system.

No direct correlation between plasma concentration and efficacy has been established. The duration of drug effect is presumed to be dependent on the rate of enzyme re-synthesis rather than on the rate of elimination of the drug from the systemic circulation.

12.2 Pharmacodynamics

Effects on Electrocardiogram
There is no indication of a QT/QTc prolonging effect of SABRIL in single doses up to 6.0 g. In a randomized, placebo-controlled, crossover study, 58 healthy subjects were administered a single oral dose of SABRIL (3 g and 6 g) and placebo. Peak concentrations for 6.0 g SABRIL were approximately 2-fold higher than the peak concentrations following the 3.0 g single oral dose.

12.3 Pharmacokinetics

Vigabatrin displayed linear pharmacokinetics after administration of single doses ranging from 0.5 g to 4 g, and after administration of repeated doses of 0.5 g and 2.0 g twice daily. Bioequivalence has been established between the oral solution and tablet formulations. The following PK information (Tmax, half-life, and clearance) of vigabatrin was obtained from stand-alone PK studies and population PK analyses.

Absorption
Following oral administration, vigabatrin is essentially completely absorbed. The time to maximum concentration (Tmax) is approximately 1 hour for children and adolescents (3 years to 16 years of age) and adults, and approximately 2.5 hours for infants (5 months to 2 years of age). There was little accumulation with multiple dosing in adult and pediatric patients. A food effect study involving administration of vigabatrin to healthy volunteers under fasting and fed conditions indicated that the Cmax was decreased by 33%, Tmax was increased to 2 hours, and AUC was unchanged under fed conditions.

Distribution
Vigabatrin does not bind to plasma proteins. Vigabatrin is widely distributed throughout the body; mean steady-state volume of distribution is 1.1 L/kg (CV = 20%).

Metabolism and Elimination
Vigabatrin is not significantly metabolized; it is eliminated primarily through renal excretion. The terminal half-life of vigabatrin is about 5.7 hours for infants (5 months to 2 years of age), 6.8 hours for children (3 to 9 years of age), 9.5 hours for children and adolescents (10 to 16 years of age), and 10.5 hours for adults. Following administration of [14]C-vigabatrin to healthy male volunteers, about 95% of total radioactivity was recovered in the urine over 72 hours with the parent drug representing about 80% of this. Vigabatrin induces CYP2C9, but does not induce other hepatic cytochrome P450 enzyme systems.

Specific Populations

Geriatric
The renal clearance of vigabatrin in healthy elderly patients (≥65 years of age) was 36% less than those in healthy younger patients. This finding is confirmed by an analysis of data from a controlled clinical trial [see Use in Specific Populations (8.5)].

Pediatric
The clearance of vigabatrin is 2.4 L/hr for infants (5 months to 2 years of age), 5.1 L/hr for children (3 to 9 years of age), 5.8 L/hr for children and adolescents (10 to 16 years of age) and 7 L/hr for adults.

Gender
No gender differences were observed for the pharmacokinetic parameters of vigabatrin in patients.

Race
No specific study was conducted to investigate the effects of race on vigabatrin pharmacokinetics. A cross study comparison between 23 Caucasian and 7 Japanese patients who received 1, 2, and 4 g of vigabatrin indicated that the AUC, Cmax, and half-life were similar for the two populations. However, the mean renal clearance of Caucasians (5.2 L/hr) was about 25% higher than the Japanese (4.0 L/hr). Inter-subject variability in renal clearance was 20% in Caucasians and was 30% in Japanese.

Renal Impairment
Mean AUC increased by 30% and the terminal half-life increased by 55% (8.1 hr vs 12.5 hr) in adult patients with mild renal impairment (CLcr from >50 to 80 mL/min) in comparison to normal subjects.

Mean AUC increased by two-fold and the terminal half-life increased by two-fold in adult patients with moderate renal impairment (CLcr from >30 to 50 mL/min) in comparison to normal subjects.

Mean AUC increased by 4.5-fold and the terminal half-life increased by 3.5-fold in adult patients with severe renal impairment (CLcr from >10 to 30 mL/min) in comparison to normal subjects.

Adult patients with renal impairment
Dosage adjustment, including starting at a lower dose, is recommended for adult patients with any degree of renal impairment [see Use in Specific Populations (8.6) and Dosage and Administration (2.4)].

Infants with renal impairment
Information about how to adjust the dose in infants with renal impairment is unavailable.

Pediatric patients 2 years and older with renal impairment
Although information is unavailable on the effects of renal impairment on vigabatrin clearance in pediatric patients 2 years and older, dosing can be calculated based upon adult data and an established formula [see Use in Specific Populations (8.6) and Dosage and Administration (2.4)].

Hepatic Impairment
Vigabatrin is not significantly metabolized. The pharmacokinetics of vigabatrin in patients with impaired liver function has not been studied.

Drug Interactions

Phenytoin
A 16% to 20% average reduction in total phenytoin plasma levels was reported in adult controlled clinical studies. In vitro drug metabolism studies indicate that decreased phenytoin concentrations upon addition of vigabatrin therapy are likely to be the result of induction of cytochrome P450 2C enzymes in some patients. Although phenytoin dose adjustments are not routinely required, dose adjustment of phenytoin should be considered if clinically indicated [see Drug Interactions (7.1)].

Clonazepam
In a study of 12 healthy adult volunteers, clonazepam (0.5 mg) co-administration had no effect on SABRIL (1.5 g twice daily) concentrations. SABRIL increases the mean Cmax of clonazepam by 30% and decreases the mean Tmax by 45% [see Drug Interactions (7.1)].

Other AEDs
When co-administered with vigabatrin, phenobarbital concentration (from phenobarbital or primidone) was reduced by an average of 8% to 16%, and sodium valproate plasma concentrations were reduced by an average of 8%. These reductions did not appear to be clinically relevant. Based on population pharmacokinetics, carbamazepine, clorazepate, primidone, and sodium valproate appear to have no effect on plasma concentrations of vigabatrin [see Drug Interactions (7.1)].

Alcohol
Co-administration of ethanol (0.6 g/kg) with vigabatrin (1.5 g twice daily) indicated that neither drug influences the pharmacokinetics of the other.

Oral Contraceptives
In a double-blind, placebo-controlled study using a combination oral contraceptive containing 30 mcg ethinyl estradiol and 150 mcg levonorgestrel, vigabatrin (3 g/day) did not interfere significantly with the cytochrome P450 isoenzyme (CYP3A)-mediated metabolism of the contraceptive tested. Based on this study, vigabatrin is unlikely to affect the efficacy of steroid oral contraceptives. Additionally, no significant difference in pharmacokinetic parameters (elimination half-life, AUC, Cmax, apparent oral clearance, time to peak, and apparent volume of distribution) of vigabatrin were found after treatment with ethinyl estradiol and levonorgestrel [see Drug Interactions (7.2)].

13 NONCLINICAL TOXICOLOGY

13.1 Carcinogenesis, Mutagenesis, Impairment of Fertility

Vigabatrin showed no carcinogenic potential in mouse or rat when given in the diet at doses up to 150 mg/kg/day for 18 months (mouse) or at doses up to 150 mg/kg/day for 2 years (rat). These doses are less than the maximum recommended human dose (MRHD) for infantile spasms (150 mg/kg/day) and for refractory complex partial seizures (3 g/day) on a mg/m^2 basis.

Vigabatrin was negative in in vitro (Ames, CHO/HGPRT mammalian cell forward gene mutation, chromosomal aberration in rat lymphocytes) and in in vivo (mouse bone marrow micronucleus) assays.

No adverse effects on male or female fertility were observed in rats at oral doses up to 150 mg/kg/day (approximately 1/2 the MRHD of 3 g/day on a mg/m^2 basis for refractory complex partial seizures).

14 CLINICAL STUDIES

14.1 Complex Partial Seizures

Adults

The effectiveness of SABRIL as adjunctive therapy in adult patients was established in two U.S. multicenter, double-blind, placebo-controlled, parallel-group clinical studies. A total of 357 adults (age 18 to 60 years) with complex partial seizures, with or without secondary generalization were enrolled (Studies 1 and 2). Patients were required to be on an adequate and stable dose of an anticonvulsant, and have a history of failure on an adequate regimen of carbamazepine or phenytoin. Patients had a history of about 8 seizures per month (median) for about 20 years (median) prior to entrance into the study. These studies were not capable by design of demonstrating direct superiority of SABRIL over any other anticonvulsant added to a regimen to which the patient had not adequately responded. Further, in these studies patients had previously been treated with a limited range of anticonvulsants.

The primary measure of efficacy was the patient’s reduction in mean monthly frequency of complex partial seizures plus partial seizures secondarily generalized at end of study compared to baseline.

Study 1

Study 1 (N=174) was a randomized, double-blind, placebo-controlled, dose-response study consisting of an 8-week baseline period followed by an 18-week treatment period. Patients were randomized to receive placebo or 1, 3, or 6 g/day vigabatrin administered twice daily. During the first 6 weeks following randomization, the dose was titrated upward beginning with 1 g/day and increasing by 0.5 g/day on days 1 and 5 of each subsequent week in the 3 g/day and 6 g/day groups, until the assigned dose was reached.

Results for the primary measure of effectiveness, reduction in monthly frequency of complex partial seizures, are shown in Table 8. The 3 g/day and 6 g/day dose groups were statistically significantly superior to placebo, but the 6 g/day dose was not superior to the 3 g/day dose.

Table 8. Median Monthly Frequency of Complex Partial Seizures^+
 | N | Baseline | Endstudy
Placebo | 45 | 9.0 | 8.8
1 g/day SABRIL | 45 | 8.5 | 7.7
3 g/day SABRIL | 41 | 8.5 | 3.7*
6 g/day SABRIL | 43 | 8.5 | 4.5*
*p<0.05 compared to placebo
^+Including one patient with simple partial seizures with secondary generalization only

Figure 1 presents the percentage of patients (X-axis) with a percent reduction in seizure frequency (responder rate) from baseline to the maintenance phase at least as great as that represented on the Y-axis. A positive value on the Y-axis indicates an improvement from baseline (i.e., a decrease in complex partial seizure frequency), while a negative value indicates a worsening from baseline (i.e., an increase in complex partial seizure frequency). Thus, in a display of this type, a curve for an effective treatment is shifted to the left of the curve for placebo. The proportion of patients achieving any particular level of reduction in complex partial seizure frequency was consistently higher for the SABRIL 3 and 6 g/day groups compared to the placebo group. For example, 51% of patients randomized to SABRIL 3 g/day and 53% of patients randomized to SABRIL 6 g/day experienced a 50% or greater reduction in seizure frequency, compared to 9% of patients randomized to placebo. Patients with an increase in seizure frequency >100% are represented on the Y-axis as equal to or greater than -100%.

Figure 1. Percent Reduction from Baseline in Seizure Frequency

Study 2

Study 2 (N=183 randomized, 182 evaluated for efficacy) was a randomized, double-blind, placebo-controlled, parallel study consisting of an 8-week baseline period and a 16-week treatment period. During the first 4 weeks following randomization, the dose of vigabatrin was titrated upward beginning with 1 g/day and increased by 0.5 g/day on a weekly basis to the maintenance dose of 3 g/day.

Results for the primary measure of effectiveness, reduction in monthly complex partial seizure frequency, are shown in Table 9. Vigabatrin 3 g/day was statistically significantly superior to placebo in reducing seizure frequency.

Table 9. Median Monthly Frequency of Complex Partial Seizures
 | N | Baseline | Endstudy
Placebo | 90 | 9.0 | 7.5
3 g/day SABRIL | 92 | 8.3 | 5.5*
*p<0.05 compared to placebo

Figure 2 presents the percentage of patients (X-axis) with a percent reduction in seizure frequency (responder rate) from baseline to the maintenance phase at least as great as that represented on the Y-axis. A positive value on the Y-axis indicates an improvement from baseline (i.e., a decrease in complex partial seizure frequency), while a negative value indicates a worsening from baseline (i.e., an increase in complex partial seizure frequency). Thus, in a display of this type, a curve for an effective treatment is shifted to the left of the curve for placebo. The proportion of patients achieving any particular level of reduction in seizure frequency was consistently higher for the SABRIL 3 g/day group compared to the placebo group. For example, 39% of patients randomized to SABRIL (3 g/day) experienced a 50% or greater reduction in complex partial seizure frequency, compared to 21% of patients randomized to placebo. Patients with an increase in seizure frequency >100% are represented on the Y-axis as equal to or greater than -100%.

Figure 2. Percent Reduction from Baseline in Seizure Frequency

For both studies, there was no difference in the effectiveness of vigabatrin between male and female patients. Analyses of age and race were not possible as nearly all patients were between the ages of 18 to 65 and Caucasian.

Pediatric patients 3 to 16 years of age

SABRIL was studied in three double-blind, placebo-controlled, parallel-group studies in 269 patients who received SABRIL and 104 patients who received placebo. No individual study was considered adequately powered to determine efficacy in pediatric patients age 3 years and above. The data from all three pediatric studies were pooled and used in a pharmacometric bridging analysis using weight-normalized doses to establish efficacy and determine appropriate dosing. All three studies were randomized, double-blind, placebo-controlled, parallel-group, adjunctive-treatment studies in patients aged 3-16 years with uncontrolled complex partial seizures with or without secondary generalization. The study period included a 6 to 10 week baseline phase and a 14 to 17 week treatment phase (composed of a titration and maintenance period).

The pharmacometric bridging approach consisted of defining a weight-normalized dose-response, and showing that a similar dose-response relationship exists between pediatric patients and adults patients when SABRIL was given as adjunctive therapy for complex partial seizures. Dosing recommendations in pediatric patients 2 to 16 years of age were derived from simulations utilizing these pharmacometric dose-response analyses [see Dosage and Administration (2.2)].

14.2 Infantile Spasms

The effectiveness of SABRIL as monotherapy was established for infantile spasms in two multicenter controlled studies. Both studies were similar in terms of disease characteristics and prior treatments of patients and all enrolled infants had a confirmed diagnosis of infantile spasms.

Study 1

Study 1 (N=221) was a multicenter, randomized, low-dose high-dose, parallel-group, partially-blind (caregivers knew the actual dose but not whether their child was classified as low or high dose; EEG reader was blinded but investigators were not blinded) study to evaluate the safety and efficacy of vigabatrin in patients <2 years of age with new-onset infantile spasms. Patients with both symptomatic and cryptogenic etiologies were studied. The study was comprised of two phases. The first phase was a 14 to 21 day partially-blind phase in which patients were randomized to receive either low-dose (18-36 mg/kg/day) or high-dose (100-148 mg/kg/day) vigabatrin. Study drug was titrated over 7 days, followed by a constant dose for 7 days. If the patient became spasm-free on or before day 14, another 7 days of constant dose was administered. The primary efficacy endpoint of this study was the proportion of patients who were spasm-free for 7 consecutive days beginning within the first 14 days of vigabatrin therapy. Patients considered spasm-free were defined as those patients who remained free of spasms (evaluated according to caregiver response to direct questioning regarding spasm frequency) and who had no indication of spasms or hypsarrhythmia during 8 hours of CCTV EEG recording (including at least one sleep-wake-sleep cycle) performed within 3 days of the seventh day of spasm freedom and interpreted by a blinded EEG reader. Seventeen patients in the high-dose group achieved spasm freedom compared with 8 patients in the low dose group. This difference was statistically significant (p=0.0375). Primary efficacy results are shown in Table 10.

Table 10. Spasm Freedom by Primary Criteria (Study 1)
 |  | SABRIL Treatment Group
 |  | 18-36 mg/kg/day [N=114] n (%) | 100-148 mg/kg/day [N=107] n (%)
Patients who Achieved Spasm Freedom |  | 8 (7.0) | 17 (15.9)
p=0.0375
Note: Primary criteria were evaluated based on caregiver assessment plus CCTV EEG confirmation within 3 days of the seventh day of spasm freedom.

Study 2

Study 2 (N=40) was a multicenter, randomized, double-blind, placebo-controlled, parallel-group study consisting of a pre-treatment (baseline) period of 2-3 days, followed by a 5-day double-blind treatment phase during which patients were treated with vigabatrin (initial dose of 50 mg/kg/day with titration allowed to 150 mg/kg/day) or placebo. The primary efficacy endpoint in this study was the average percent change in daily spasm frequency, assessed during a pre-defined and consistent 2-hour window of evaluation, comparing baseline to the final 2 days of the 5-day double-blind treatment phase. No statistically significant differences were observed in the average frequency of spasms using the 2-hour evaluation window. However, a post-hoc alternative efficacy analysis, using a 24-hour clinical evaluation window found a statistically significant difference in the overall percentage of reductions in spasms between the vigabatrin group (68.9%) and the placebo group (17.0%) (p=0.030).

Duration of therapy for infantile spasms was evaluated in a post hoc analysis of a Canadian Pediatric Epilepsy Network (CPEN) study of developmental outcomes in infantile spasms patients. The 38/68 infants in the study who had responded to vigabatrin therapy (complete cessation of spasms and hypsarrhythmia) continued vigabatrin therapy for a total duration of 6 months therapy. The 38 infants who responded were then followed for an additional 18 months after discontinuation of vigabatrin to determine their clinical outcome. A post hoc analysis indicated no observed recurrence of infantile spasms in any of these 38 infants.

16 HOW SUPPLIED/STORAGE AND HANDLING

16.1 How Supplied

SABRIL 500 mg tablets are white, film-coated, oval, biconvex, scored on one side, and debossed with OV 111 on the other. They are supplied as bottles of 100 (NDC 67386-111-01).

SABRIL for oral solution is available as 500 mg packets containing a white to off-white granular powder. They are supplied in packages of 50 (NDC 67386-211-65).

The oral syringes are provided separately by the pharmacy.

16.2 Storage and Handling

Store at 20°C to 25°C (68°F to 77°F). See USP controlled room temperature.

17 PATIENT COUNSELING INFORMATION

Advise patients and caregivers to read the FDA-approved patient labeling (Medication Guide and Instructions for Use).

Administration Instructions for SABRIL for oral solution

Physicians should confirm that caregivers(s) understand how to mix SABRIL for oral solution and to administer the correct dose to their infants and pediatric patients [see Dosage and Administration (2.5)].

Permanent Vision Loss
Inform patients and caregivers of the risk of permanent vision loss, particularly loss of peripheral vision, from SABRIL, and the need for monitoring vision [see Warnings and Precautions (5.1)].

Monitoring of vision, including assessment of visual fields and visual acuity, is recommended at baseline (no later than 4 weeks after starting SABRIL), at least every 3 months while on therapy, and about 3-6 months after discontinuation of therapy. In patients for whom vision testing is not possible, treatment may continue without recommended testing according to clinical judgment with appropriate patient or caregiver counseling. Patients or caregivers should be informed that if baseline or subsequent vision is not normal, SABRIL should only be used if the benefits of SABRIL treatment clearly outweigh the risks of additional vision loss.

Advise patients and caregivers that vision testing may be insensitive and may not detect vision loss before it is severe. Also advise patients and caregivers that if vision loss is documented, such loss is irreversible. Ensure that both of these points are understood by patients and caregivers.

Patients and caregivers should be informed that if changes in vision are suspected, they should notify their physician immediately.

Vigabatrin REMS Program
SABRIL is available only through a restricted program called the Vigabatrin REMS Program [see Warnings and Precautions (5.2)]. Inform patients/caregivers of the following:

- Patients/caregivers must be enrolled in the program.
- SABRIL is only available through pharmacies that are enrolled in the Vigabatrin REMS Program.

MRI Abnormalities in Infants
Inform caregiver(s) of the possibility that infants may develop an abnormal MRI signal of unknown clinical significance [see Warnings and Precautions (5.3)].

Suicidal Thinking and Behavior
Counsel patients, their caregiver(s), and families that AEDs, including SABRIL, may increase the risk of suicidal thoughts and behavior. Also advise patients and caregivers of the need to be alert for the emergence or worsening of symptoms of depression, any unusual changes in mood or behavior, or the emergence of suicidal thoughts, behavior, or thoughts of self-harm. Behaviors of concern should be reported immediately to healthcare providers [see Warnings and Precautions (5.5)].

Pregnancy

Advise pregnant women and women of child-bearing potential that the use of SABRIL during pregnancy can cause fetal harm which may occur early in pregnancy before many women know they are pregnant. Instruct patients to notify their physician if they become pregnant or intend to become pregnant during therapy. Advise patients that there is a pregnancy exposure registry that collects information about the safety of antiepileptic drugs during pregnancy [see Use in Specific Populations (8.1)].

Nursing

Counsel patients that SABRIL is excreted in breast milk. Because of the potential for serious adverse reactions in nursing infants from SABRIL, breastfeeding is not recommended. If a decision is made to breastfeed, nursing mothers should be counseled to observe their infants for signs of vision loss, sedation and poor sucking [see Use in Specific Populations (8.2)].

Withdrawal of SABRIL Therapy
Instruct patients and caregivers not to suddenly discontinue SABRIL therapy without consulting with their healthcare provider. As with all AEDs, withdrawal should be gradual [see Warnings and Precautions (5.6)].

Manufactured by: Patheon
Cincinnati, OH 45237, U.S.A.

For: Lundbeck
Deerfield, IL 60015, U.S.A.

SABRIL is a registered trademark of Lundbeck

MEDICATION GUIDE

SABRIL® (SAY-bril)
(vigabatrin)
tablets

SABRIL® (SAY-bril)
(vigabatrin)
for oral solution

What is the most important information I should know about SABRIL?

SABRIL can cause serious side effects, including:

- Permanent vision loss
- Magnetic resonance imaging (MRI) changes in babies with infantile spasms (IS)
- Risk of suicidal thoughts or actions

1. Permanent vision loss:

SABRIL can damage the vision of anyone who takes it. Some people can have severe loss particularly to their ability to see to the side when they look straight ahead (peripheral vision). With severe vision loss, you may only be able to see things straight in front of you (sometimes called “tunnel vision”). You may also have blurry vision. If this happens, it will not get better.

- Vision loss and use of SABRIL in adults and children 2 years and older: Because of the risk of vision loss, SABRIL is used to treat complex partial seizures (CPS) only in people who do not respond well enough to several other medicines.

Tell your healthcare provider right away if you (or your child):

- might not be seeing as well as before starting SABRIL.
- start to trip, bump into things, or are more clumsy than usual.
- are surprised by people or things coming in front of you that seem to come out of nowhere.

- These changes can mean that you (or your child) have damage to your vision.
- It is recommended that your healthcare provider test your (or your child’s) vision (including peripheral vision) and visual acuity (ability to read an eye chart) before you (or your child) start SABRIL or within 4 weeks after starting SABRIL, and at least every 3 months after that until SABRIL is stopped. It is also recommended that you (or your child) have a vision test about 3 to 6 months after SABRIL is stopped. Your vision loss may get worse after you stop taking Sabril.
- Some people are not able to complete testing of vision. Your healthcare provider will determine if you (or your child) can be tested. If you (or your child) cannot complete vision testing, your healthcare provider may continue prescribing SABRIL, but your healthcare provider will not be able to watch for any vision loss you (or your child) may get.
- Even if your vision (or your child’s vision) seems fine, it is important that you (or your child) get these regular vision tests because vision damage can happen before you (or your child) notice any changes.
- These vision tests cannot prevent the vision damage that can happen with SABRIL, but they do allow the healthcare provider to decide if you (or your child) should stop SABRIL if your vision has gotten worse.
- Vision testing may not detect vision loss before it is severe.
- If you do not have these vision tests regularly, your healthcare provider may stop prescribing SABRIL.
- If you drive and your vision is damaged by SABRIL, driving might be more dangerous, or you may not be able to drive safely at all. Talk about this with your healthcare provider.
- Vision loss in babies: Because of the risk of vision loss, SABRIL is used in babies 1 month to 2 years of age with infantile spasms (IS) only when you and your healthcare provider decide that the possible benefits of SABRIL are more important than the risks.

- Parents or caregivers are not likely to recognize the symptoms of vision loss in babies until it is severe. Healthcare providers may not find vision loss in babies until it is severe.
- It is difficult to test vision in babies, but, to the extent possible, all babies should have their vision tested before starting SABRIL or within 4 weeks after starting SABRIL, and every 3 months after that until SABRIL is stopped. Your baby should also have a vision test about 3 to 6 months after SABRIL is stopped.
- Your baby may not be able to be tested. Your healthcare provider will determine if your baby can be tested. If your baby cannot be tested, your healthcare provider may continue prescribing SABRIL, but your healthcare provider will not be able to watch for any vision loss.

Tell your healthcare provider right away if you think that your baby is:

- not seeing as well as before taking SABRIL.
- acting differently than normal.

- Even if your baby’s vision seems fine, it is important to get regular vision tests because damage can happen before your baby acts differently. Even these regular vision exams may not show the damage to your baby’s vision before it is severe and permanent.

All people who take SABRIL:

- You are at risk for permanent vision loss with any amount of SABRIL.
- Your risk of vision loss may be higher the more SABRIL you take daily and the longer you take it.
- It is not possible for your healthcare provider to know when vision loss will happen. It could happen soon after starting SABRIL or any time during treatment. It may even happen after treatment has stopped.

- Because SABRIL might cause permanent vision loss, it is available to healthcare providers and patients only under a special program called the Vigabatrin Risk Evaluation and Mitigation Strategy (REMS) Program. SABRIL can only be prescribed to people who are enrolled in this program. As part of the Vigabatrin REMS Program, it is recommended that your healthcare provider test your (or your child’s) vision from time to time (periodically) while you (or your child) are being treated with SABRIL, and even after you (or your child) stop treatment. Your healthcare provider will explain the details of the Vigabatrin REMS Program to you. For more information, go to www.vigabatrinREMS.com or call 1-866-244-8175.

2. Magnetic resonance imaging (MRI) changes in babies with infantile spasms:

Brain pictures taken by magnetic resonance imaging (MRI) show changes in some babies after they are given SABRIL. It is not known if these changes are harmful.

3. Risk of suicidal thoughts or actions:

Like other antiepileptic drugs, SABRIL may cause suicidal thoughts or actions in a very small number of people, about 1 in 500 people taking it. Call a healthcare provider right away if you or your child have any of these symptoms, especially if they are new, worse, or worry you:

- thoughts about suicide or dying
- attempts to commit suicide
- new or worse depression
- new or worse anxiety
- feeling agitated or restless
- panic attacks
- trouble sleeping (insomnia)
- new or worse irritability
- acting aggressive, being angry, or violent
- acting on dangerous impulses
- an extreme increase in activity and talking (mania)
- other unusual changes in behavior or mood

Suicidal thoughts or actions can be caused by things other than medicines. If you or your child have suicidal thoughts or actions, your healthcare provider may check for other causes.

How can I watch for early symptoms of suicidal thoughts and actions?

- Pay attention to any changes, especially sudden changes, in mood, behaviors, thoughts, or feelings.
- Keep all follow-up visits with your healthcare provider as scheduled.
- Call your healthcare provider between visits as needed, especially if you are worried about symptoms.
- Do not stop SABRIL without first talking to a healthcare provider.
- Stopping SABRIL suddenly can cause serious problems. Stopping a seizure medicine suddenly can cause seizures that will not stop (status epilepticus) in people who are being treated for seizures.

What is SABRIL?

- SABRIL is a prescription medicine used along with other treatments to treat adults and children 2 years and older with complex partial seizures (CPS) if:
  ○ the CPS do not respond well enough to several other treatments, and
  ○ you and your healthcare provider decide the possible benefit of taking SABRIL is more important than the risk of vision loss.
  SABRIL should not be the first medicine used to treat CPS.

- SABRIL is also used to treat babies 1 month to 2 years of age who have infantile spasms (IS) if you and your healthcare provider decide the possible benefits of taking SABRIL are more important than the possible risk of vision loss.

What should I tell my healthcare provider before starting SABRIL?

If you or your child has CPS, before taking SABRIL tell your healthcare provider about all of your medical conditions, including if you or your child:

- have or had an allergic reaction to SABRIL, such as hives, itching, or trouble breathing.
- have or had any vision problems.
- have or had any kidney problems.
- have or had low red blood cell counts (anemia).
- have or had any nervous or mental illnesses such as depression, mood problems, thoughts of suicide, or attempts at suicide.
- are breastfeeding or planning to breastfeed. SABRIL can pass into breast milk and may harm your baby. Talk to your healthcare provider about the best way to feed your baby if you take SABRIL.
- are pregnant or plan to become pregnant. SABRIL can cause harm to your unborn baby. You and your healthcare provider will have to decide if you should take SABRIL while you are pregnant.

Pregnancy Registry:

If you become pregnant while taking SABRIL, talk to your healthcare provider about registering with the North American Antiepileptic Drug Pregnancy Registry. You can enroll in this registry by calling 1-888-233-2334. Information on the registry can also be found at the website http://www.aedpregnancyregistry.org/. The purpose of this registry is to collect information about the safety of antiepileptic medicine during pregnancy.

If you are a parent or caregiver whose baby has IS, before giving SABRIL to your baby, tell your healthcare provider about all of your baby’s medical conditions, including if your baby has or ever had:

- an allergic reaction to SABRIL, such as hives, itching, or trouble breathing.
- any vision problems.
- any kidney problems.

Tell your healthcare provider about all the medicines you or your child take, including prescription and over-the-counter medicines, vitamins, and herbal supplements. SABRIL and other medicines may affect each other causing side effects.

How should I take SABRIL?

- SABRIL comes as tablets or as packets containing powder for mixing with water to make an oral solution.
- You or your child will receive SABRIL from a specialty pharmacy.
- Take SABRIL exactly as your healthcare provider tells you to. SABRIL is usually taken 2 times each day.
- SABRIL may be taken with or without food.
- Before starting to take SABRIL, talk to your healthcare provider about what you or your child should do if a SABRIL dose is missed.
- If you or your child are taking SABRIL for CPS and the seizures do not improve enough within 3 months, your healthcare provider will stop prescribing SABRIL.
- If your child is taking SABRIL for IS and the seizures do not improve within 2 to 4 weeks, your healthcare provider will stop prescribing SABRIL.
- Do not stop taking SABRIL suddenly. This can cause serious problems. Stopping SABRIL or any seizure medicine suddenly can cause seizures that will not stop (status epilepticus) in people who are being treated for seizures. You should follow your healthcare provider’s instructions on how to stop taking SABRIL.
- Tell your healthcare provider right away about any increase in seizures when SABRIL treatment is being stopped. Before your child starts taking SABRIL, speak to your child’s healthcare provider about what to do if your baby misses a dose, vomits, spits up, or only takes part of the dose of SABRIL.
- Do not stop taking SABRIL without talking to your healthcare provider. If SABRIL improves your (or your child’s) seizures, you and your healthcare provider should talk about whether the benefit of taking SABRIL is more important than the risk of vision loss, and decide if you (or your child) will continue to take SABRIL.
- If you are giving SABRIL for oral solution to your child, it can be given at the same time as their meal. SABRIL powder should be mixed with water only.
- See “Instructions for Use” for detailed information about how to mix and give SABRIL for oral solution to your child the right way.

What should I avoid while taking SABRIL?

SABRIL causes sleepiness and tiredness. Adults taking SABRIL should not drive, operate machinery, or perform any hazardous task, unless you and your healthcare provider have decided that you can do these things safely.

What are the possible side effects of SABRIL?

SABRIL can cause serious side effects, including:

- See “What is the most important information I should know about SABRIL?”
- sleepiness and tiredness. See “What should I avoid while taking SABRIL?”
- SABRIL may cause your baby to be sleepy. Sleepy babies may have a harder time suckling and feeding, or may be irritable.
- weight gain that happens without swelling.

The following serious side effects happen in adults. It is not known if these side effects also happen in babies who take SABRIL.

- low red blood cell counts (anemia).
- nerve problems. Symptoms of a nerve problem can include numbness and tingling in your toes or feet. It is not known if nerve problems will go away after you stop taking SABRIL.
- swelling.

If you or your child has CPS, SABRIL may make certain types of seizures worse. Tell your healthcare provider right away if your (or your child's) seizures get worse.

The most common side effect of SABRIL in adults include blurred vision, sleepiness, dizziness, problems walking or feeling uncoordinated, shaking (tremor), and tiredness.

The most common side effect of SABRIL in children 3 to 16 years of age is weight gain. Also expect side effects like those seen in adults.

If you are giving SABRIL to your baby for IS:

SABRIL may make certain types of seizures worse. You should tell your baby’s healthcare provider right away if your baby’s seizures get worse. Tell your baby’s healthcare provider if you see any changes in your baby’s behavior.

The most common side effects of SABRIL in babies include:

- sleepiness - SABRIL may cause your baby to be sleepy. Sleepy babies may have a harder time suckling and feeding or may be irritable.
- swelling in the bronchial tubes (bronchitis)
- ear infection
- irritability

Tell your healthcare provider if you or your child have any side effect that bothers you or that does not go away. These are not all the possible side effects of SABRIL.

Call your doctor for medical advice about side effects. You may report side effects to FDA at 1-800-FDA-1088.

How should I store SABRIL?

- Store SABRIL tablets and SABRIL packets at room temperature between 68ºF to 77ºF (20ºC to 25ºC).

Keep SABRIL and all medicines out of the reach of children.

General information about the safe and effective use of SABRIL.

Medicines are sometimes prescribed for purposes other than those listed in a Medication Guide. You can ask your pharmacist or healthcare provider for information about SABRIL that is written for health professionals. Do not use SABRIL for a condition for which it was not prescribed. Do not give SABRIL to other people, even if they have the same symptoms that you have. It may harm them.

What are the ingredients in SABRIL?
Active Ingredient: vigabatrin
Inactive Ingredients:

- Tablets: hydroxypropyl methylcellulose, magnesium stearate, microcrystalline cellulose, polyethylene glycols, povidone, sodium starch glycolate, and titanium dioxide
- For oral solution: povidone

Marketed by: Lundbeck, Deerfield, IL 60015, U.S.A.

SABRIL is a registered trademark of Lundbeck

For more information, go to www.SABRIL.net or call 1-866-402-8520.

This Medication Guide has been approved by the U.S. Food and Drug Administration. Revised: 10/2021

PACKAGE LABEL

PRINCIPAL DISPLAY PANEL
NDC 67386-111-01
Sabril®
(vigabatrin) Tablets
500 mg
DISPENSE THE ENCLOSED MEDICATION
GUIDE WITH EACH PRESCTIPTION.
Rx only
100 Tablets